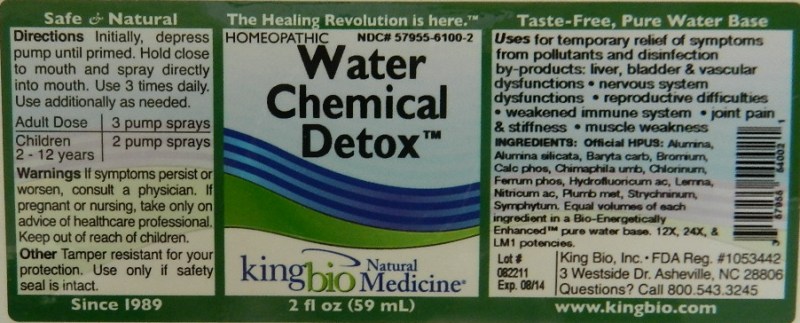 DRUG LABEL: Water Chemical Detox
NDC: 57955-6100 | Form: LIQUID
Manufacturer: King Bio Inc.
Category: homeopathic | Type: HUMAN OTC DRUG LABEL
Date: 20111121

ACTIVE INGREDIENTS: ALUMINUM OXIDE 12 [hp_X]/59 mL; KAOLIN 12 [hp_X]/59 mL; BARIUM CARBONATE 12 [hp_X]/59 mL; BROMINE  12 [hp_X]/59 mL; TRIBASIC CALCIUM PHOSPHATE 12 [hp_X]/59 mL; CHIMAPHILA UMBELLATA 12 [hp_X]/59 mL; CHLORINE 12 [hp_X]/59 mL; FERROSOFERRIC PHOSPHATE 12 [hp_X]/59 mL; HYDROFLUORIC ACID 12 [hp_X]/59 mL; LEMNA MINOR 12 [hp_X]/59 mL; NITRIC ACID 12 [hp_X]/59 mL; LEAD 12 [hp_X]/59 mL; STRYCHNINE 12 [hp_X]/59 mL; COMFREY ROOT 12 [hp_X]/59 mL
INACTIVE INGREDIENTS: WATER

Water Chemical Detox

Active Ingredient

Alumina, Alumina Silicata, Baryta Carbonica, Bromium, Calcarea Phosphorica, Chimaphila Umbellata, Chlorinum, Ferrum Phosphoricum, Hydrofluoricum Acidum, Lemna Minor, Nitricum Acidum, Plumbum Metallicum, Strychninum and Symphytum Officinale.

Reference image water detox.jpg

Inactive Ingredient

Equal volumes of each ingredient in a Bio-Energetically Enhanced pure water base. 12X, 24X and LM1 potencies.

Reference image water detox.jpg

Dosage and Administration

Directions Initially, depress pump until primed. Hold close to mouth and spray one dose directly into mouth. Use 3 times per day. Use additionally as needed.

Adult Dose 3 pump sprays

Children (2-12 years) 2 pump sprays

Reference image water detox

Warnings

If symptoms persist or worsen, or if pregnant or nursing, take only on advice of a healthcare professional. Keep out of reach of children.

Other: tamper resistant for your protection. Use only if safety seal is intact.

Reference image water detox.jpg

Keep out of reach of children.
Reference image water detox.jpg

Purpose

Uses for temporary relief of symptoms from pollutants and disinfection by-products: liver, bladder and vascular dysfunctions, nervous system dysfunctions, reproductive difficulties, weakened immune system, joint pain and stiffness, muscle weakness.

Reference image water detox.jpg

Indications and Usage

Uses for temporary relief of symptoms from pollutants and disinfection by-products:

- liver, bladder and vascular dysfunctions
- nervous system dysfunctions
- reproductive difficulties
- weakened immune system
- joint pain and stiffness
- muscle weakness

Reference image water detox.jpg

PACKAGE LABEL

King Bio, Inc.

3 Westside Drive

Asheville, NC 28806

Questions? Call 800.543.3245

www.kingbio.com

Reference image water detox.jpg